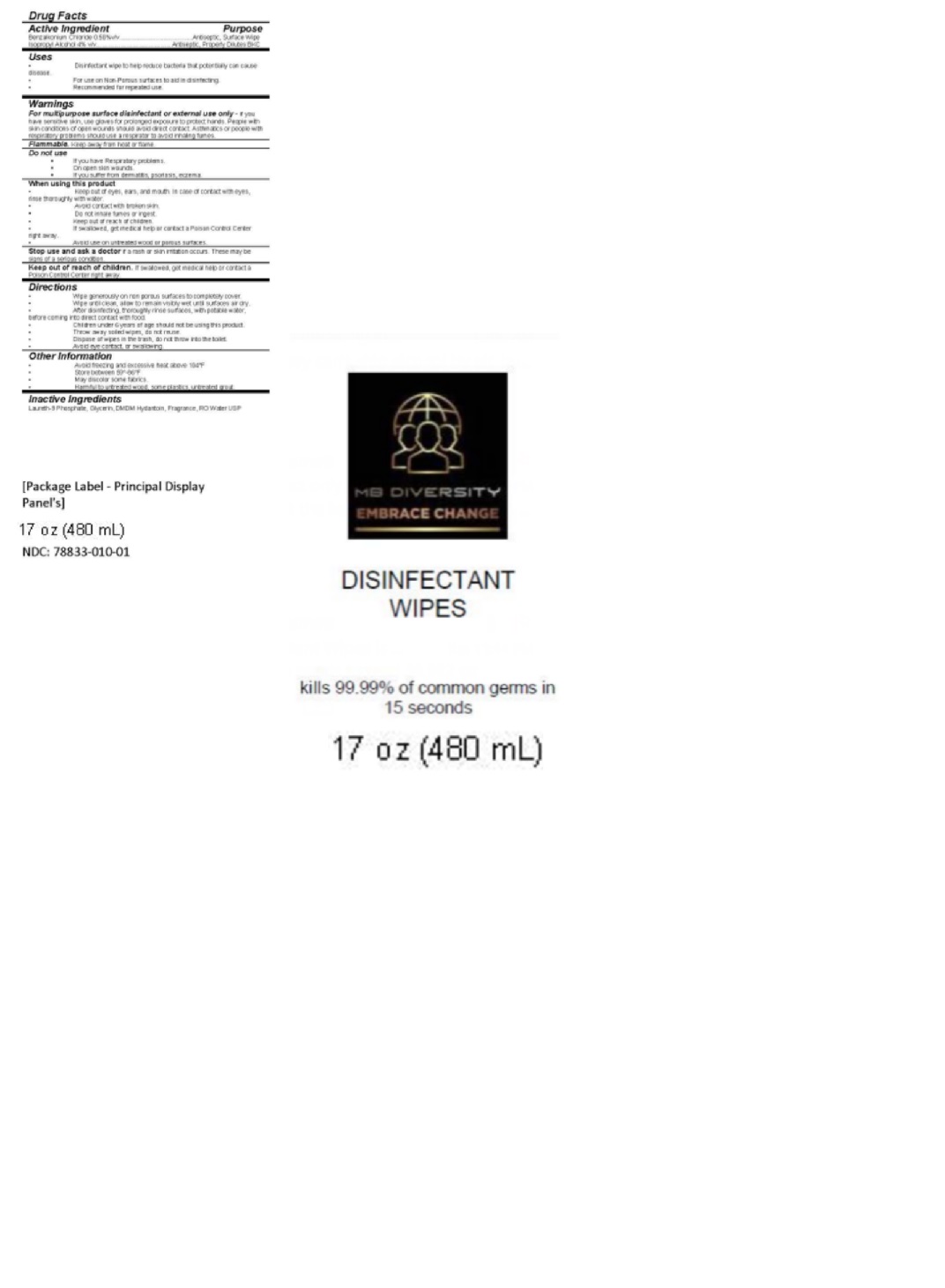 DRUG LABEL: Disinfectant Wipes
NDC: 78833-010 | Form: CLOTH
Manufacturer: MB Diversity
Category: otc | Type: HUMAN OTC DRUG LABEL
Date: 20200707

ACTIVE INGREDIENTS: ISOPROPYL ALCOHOL 4 mL/100 mL; BENZALKONIUM CHLORIDE 0.5 mg/100 mL
INACTIVE INGREDIENTS: DMDM HYDANTOIN 0.2 mL/100 mL; GLYCERIN 3 mL/100 mL; WATER 87.104 mL/100 mL; CITRONELLAL 0.016 mL/100 mL; .ALPHA.-PINENE 0.016 mL/100 mL; LINALOOL, (+)- 0.016 mL/100 mL; LINALYL ACETATE 0.02 mL/100 mL; MYRCENE 0.016 mL/100 mL; LIMONENE DIEPOXIDE 0.016 mL/100 mL; 2-METHOXY-1-PROPANOL 0.016 mL/100 mL; CITRAL 0.016 mL/100 mL; 4-METHYL-1,4-PENTANEDIYL DIMETHACRYLATE 0.016 mL/100 mL; DIPROPYLENE GLYCOL 0.016 mL/100 mL; LAURETH-9 PHOSPHATE 5 mL/100 mL; .BETA.-PINENE 0.016 mL/100 mL; TERPINOLENE 0.016 mL/100 mL

Disinfectant Wipes

OTC Monograph Not Final

This is a disinfectant wipe manufacturered according to the FDA Monograph Not Final, regarding Benzalkonium Chloride as a disinfectant, which may be used to battle COVID-19. It has proven effective at destroying coronavirus' envelopes, and many other biocide functions for years. We chose a solution of 0.50% BZK concentration to prevent any topical skin irritation, which has been documented at levels of ≥1% concentrations. We also advise anyone with skin conditions to wear gloves, or any Respiratory problems to use a sufficient Respirator, such as an N-95, because inhalation of BZK has shown complications with individuals who have severe asthma or other Respiratory Problems. We also advise rinsing disinfected surfaces with potable water before placing food on them, to prevent any unwanted ingestions of the BKS.

BKC formulation kills 99.99% of most bacteria, and also influenza as well as molds.

Less than a year ago, the Food and Drug Administration went even further, green-lighting the over-the-counter sale of BZK-manufactured hand hygiene products.

Active Ingredient(s)

Benzalkonium Chloride 0.5% v/v. Purpose Antiseptic

Alcohol 4% v/v. Purpose: Antiseptic, Necessary to Dilluted BKC

Purpose

Antiseptic, Multi Surface Disinfectant, and Topical Antiseptic

Use

Multi-surface and topical Disinfectant wipe to help reduce bacteria that potentially can cause disease.

For use on Non-Porous surfaces to aid in disinfecting.

Recommended for repeated use.

Do not use

- If you have Respiratory problems.
- On open skin wounds.
- If you suffer from dermatitis, psoriasis, excema.

When using this product

Keep out of eyes, ears, and mouth. In case of contact with eyes, rinse thoroughly with water.

Avoid contact with broken skin.

Do not inhale fumes or ingest.

Keep out of reach of children.

If swallowed, get medical help or contact a Poison Control Center right away.

Avoid use on untreated wood or porous surfaces.

Stop use and ask a doctor if irritation or rash occurs. These may be signs of a serious condition.

Keep out of reach of children. If swallowed, get medical help or contact a Poison Control Center right away.

Warnings

For external use only. Flammable. Keep away from heat or flame

Directions

- Wipe generously on non porous surfaces to completely cover.
- Wipe until clean, allow to remain visibly wet until surfaces air dry.
- After disinfecting, thoroughly rinse surfaces, with potable water, before coming into direct contact with food.
- Children under 6 years of age should not be using this product.
- Throw away soiled wipes, do not reuse.
- Dispose of wipes in the trash, do not throw into the toilet.
- Avoid eye contact, or swallowing.

Other information

- Store between 15-30C (59-86F)
- Avoid freezing and excessive heat above 40C (104F)

Inactive ingredients

Laureth-9 Phosphate, Glycerin, DMDM Hydantoin, Fragrance, RO Water USP

Drug Facts

Active Ingredient

Purpose

Benzalkonium Chloride 0.50%v/v...........................................Antiseptic, Surface Wipe

Isopropyl Alcohol 4% v/v…………………..………….. Antiseptic, Properly Dilutes BKC

Uses

Disinfectant wipe to help reduce bacteria that potentially can cause disease.

For use on Non-Porous surfaces to aid in disinfecting.

Recommended for repeated use.

Warnings

For multipurpose surface disinfectant or external use only - if you have sensitive skin, use gloves for prolonged exposure to protect hands. People with skin conditions of open wounds should avoid direct contact. Asthmatics or people with respiratory problems should use a respirator to avoid inhaling fumes.

Flammable. Keep away from heat or flame.

Do not use

If you have Respiratory problems.

On open skin wounds.

If you suffer from dermatitis, psoriasis, excema

When using this product

Keep out of eyes, ears, and mouth. In case of contact with eyes, rinse thoroughly with water.

Avoid contact with broken skin.

Do not inhale fumes or ingest.

Keep out of reach of children.

If swallowed, get medical help or contact a Poison Control Center right away.

Avoid use on untreated wood or porous surfaces.

Stop use and ask a doctor if a rash or skin irritation occurs. These may be signs of a serious condition.

Keep out of reach of children. If swallowed, get medical help or contact a Poison Control Center right away.

Directions

Wipe generously on non porous surfaces to completely cover.

Wipe until clean, allow to remain visibly wet until surfaces air dry.

After disinfecting, thoroughly rinse surfaces, with potable water, before coming into direct contact with food.

Children under 6 years of age should not be using this product.

Throw away soiled wipes, do not reuse.

Dispose of wipes in the trash, do not throw into the toilet.

Avoid eye contact, or swallowing.

Other Information

Avoid freezing and excessive heat above 104°F

Store between 59°-86°F

May discolor some fabrics

Harmful to untreated wood, some plastics, untreated grout.

Inactive Ingredients

Laureth-9 Phosphate, Glycerin, DMDM Hydantoin, Fragrance, RO Water USP

Package Label - Principal Display Panel

480 mL NDC: 78833-010-01